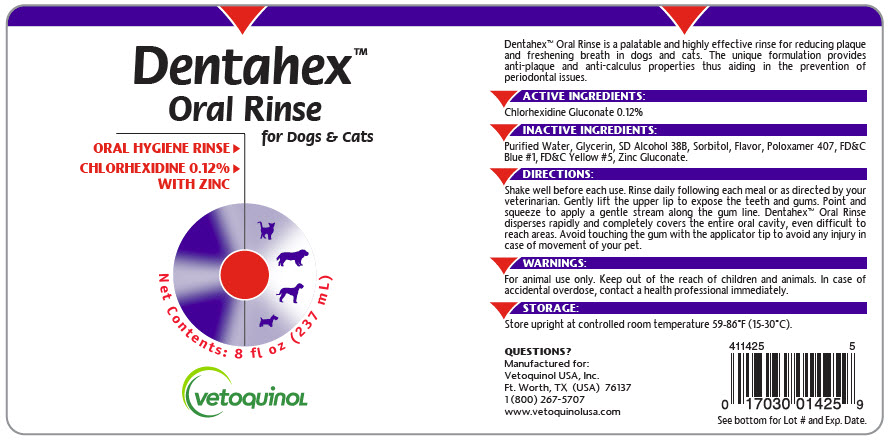 DRUG LABEL: Dentahex 
NDC: 17030-004 | Form: RINSE
Manufacturer: Vetoquinol USA, Inc.
Category: animal | Type: OTC ANIMAL DRUG LABEL
Date: 20211213

ACTIVE INGREDIENTS: CHLORHEXIDINE GLUCONATE 1.2 mg/1 mL
INACTIVE INGREDIENTS: WATER; GLYCERIN; ALCOHOL; SORBITOL; POLOXAMER 407; FD&C BLUE NO. 1; FD&C YELLOW NO. 5; ZINC GLUCONATE

Dentahex™
Oral Rinse for Dogs & Cats

VETERINARY INDICATIONS

Dentahex™ Oral Rinse is a palatable and highly effective rinse for reducing plaque and freshening breath in dogs and cats. The unique formulation provides anti-plaque and anti-calculus properties thus aiding in the prevention of periodontal issues.

ACTIVE INGREDIENTS:

Chlorhexidine Gluconate 0.12%

INACTIVE INGREDIENTS:

Purified Water, Glycerin, SD Alcohol 38B, Sorbitol, Flavor, Poloxamer 407, FD&C Blue #1, FD&C Yellow #5, Zinc Gluconate.

DIRECTIONS:

Shake well before each use. Rinse daily following each meal or as directed by your veterinarian. Gently lift the upper lip to expose the teeth and gums. Point and squeeze to apply a gentle stream along the gum line. Dentahex™ Oral Rinse disperses rapidly and completely covers the entire oral cavity, even difficult to reach areas. Avoid touching the gum with the applicator tip to avoid any injury in case of movement of your pet.

WARNINGS:

For animal use only. Keep out of the reach of children and animals. In case of accidental overdose, contact a health professional immediately.

STORAGE:

Store upright at controlled room temperature 59-86°F (15-30°C).

QUESTIONS?

Manufactured for:
Vetoquinol USA, Inc.
Ft. Worth, TX (USA) 76137
1 (800) 267-5707
www.vetoquinolusa.com

411425 6

See bottom for Lot # and Exp. Date.

PRINCIPAL DISPLAY PANEL - 237 mL Bottle Label

Dentahex™
Oral Rinse
for Dogs & Cats

ORAL HYGIENE RINSE ⏵
CHLORHEXIDINE 0.12%⏵
WITH ZINC

Net Contents: 8 fl oz (237 mL)

vetoquinoL